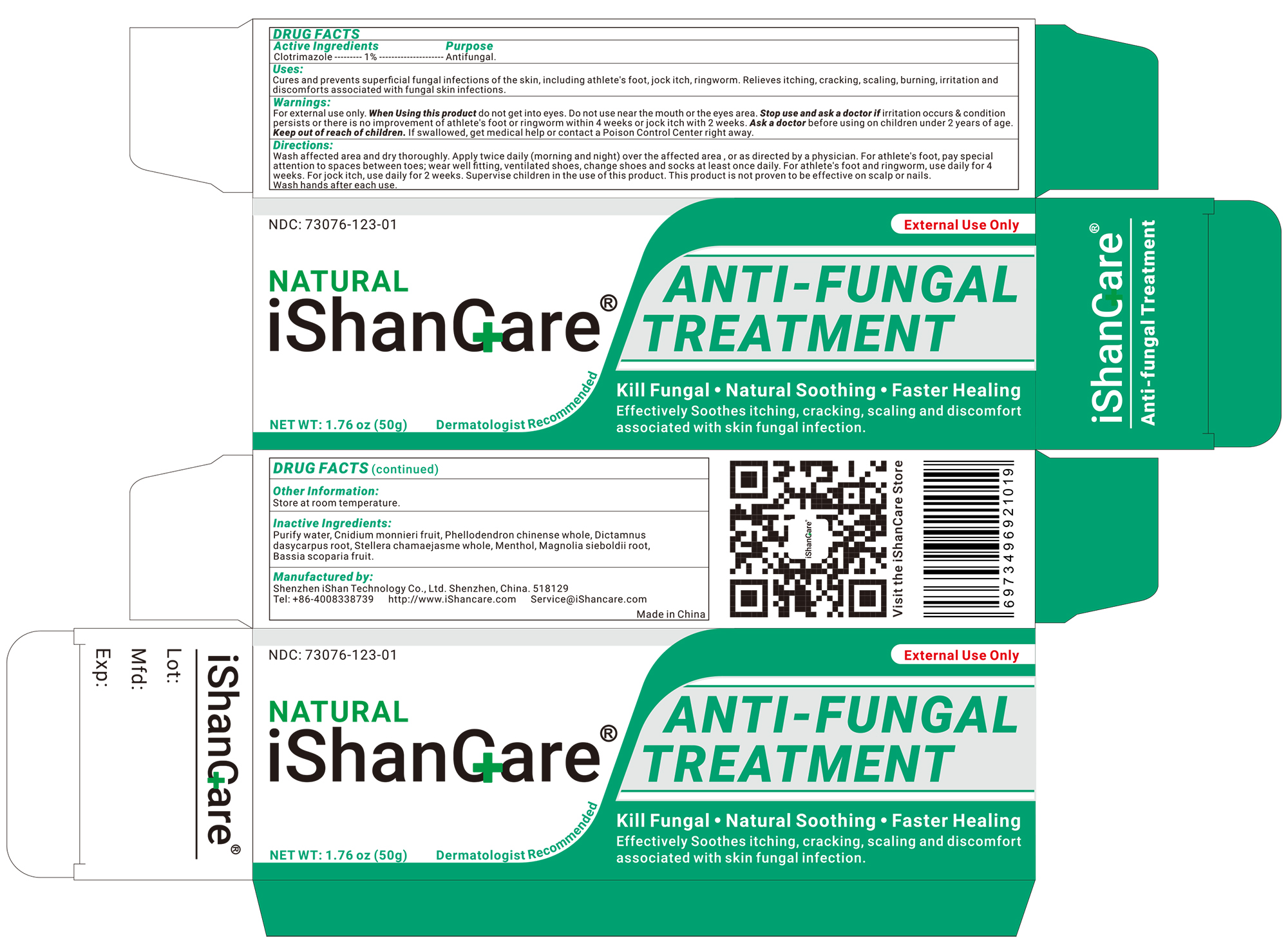 DRUG LABEL: ishancare Feminine Itch Protect
NDC: 73076-138 | Form: CREAM
Manufacturer: Shenzhen Ishan Technology Co., Ltd
Category: homeopathic | Type: HUMAN OTC DRUG LABEL
Date: 20260213

ACTIVE INGREDIENTS: OATMEAL 1 g/100 g
INACTIVE INGREDIENTS: SOPHORA FLAVESCENS ROOT 5 g/100 g; STELLERA CHAMAEJASME WHOLE 3 g/100 g; BASSIA SCOPARIA FRUIT 3 g/100 g; PHELLODENDRON CHINENSE WHOLE 5 g/100 g; DICTAMNUS DASYCARPUS ROOT 3 g/100 g; MAGNOLIA SIEBOLDII ROOT 3 g/100 g; MENTHOL 1 g/100 g; WATER

Active ingredients

Clotrimazole----1%----Antifungal

Inactive ingredients

Purify water, cnidium monnieri fruit, phellodendron chinense whole, dictamnus dasycarpus root, stellera chamaejasme whole, menthol, magnolia sieboldii root, bassia scoparia fruit.

Keep out of reach of children.

If swallowed, get medical help or contact a Poison Control Center right away.

Ask a doctor before

using on children under 2 years of age

Stop use and ask a doctor if

Irritation occurs & condition persists or there is no improvementof athlete's foot or ringworm within 4 weeks or jock intch with 2 weeks

USES

Cures and Prevents Superficial Fungal Infections of The Skin, including athlete's foot, jock itch, ringworm. Relieves itching, cracking, scaling, burning, irritation and discomforts associated with fungal skin infections.

Other information

Store at room temperature.

Directions

*Wash affected area and dry thoroughly
* Apply twice daily (morning and night) over the affected area , or as directed by a physician.
* Use daily for 4 weeks, pay special attention to the spaces between the toes; wear well-fitting ventilated shoes, and change shoes and socks at least once daily.
* For athlete's foot, pay special attention to spaces between toes; wear well fitting, ventilated shoes, change shoes and socks at least once daily.
* For athlete's foot and ringworm, use daily for 4 weeks.
* For jock itch, use daily for 2 weeks.
* Supervise children in the use of this product.
* This product is not proven to be effective on scalp or nails.
* Wash hands after each use.

Dosage & administration

Apply as needed

When Using this product

Do not get into eyes.

Warning

For external use only.